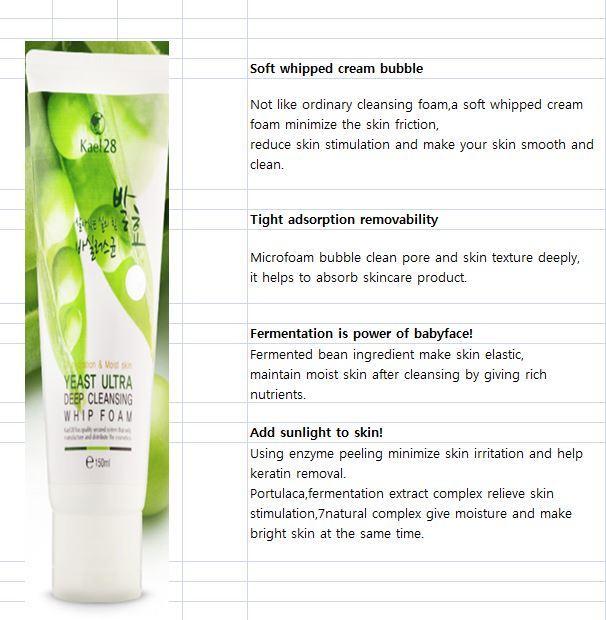 DRUG LABEL: YEAST ULTRA DEEP CLEANSING WHIP FOAM
NDC: 69663-2001 | Form: LIQUID
Manufacturer: SA Cosmetic
Category: otc | Type: HUMAN OTC DRUG LABEL
Date: 20150314

ACTIVE INGREDIENTS: GLYCERIN 16 g/100 mL
INACTIVE INGREDIENTS: WATER; DIMETHICONE; ALLANTOIN

Drug Facts

ACTIVE INGREDIENT

glycerine

INACTIVE INGREDIENT

water, dimethicone, allantoin, beeswax, panthenol, sodium hyaluronate, etc

PURPOSE

skin protectantreduce skin stimulation and make your skin smooth and clean

keep out of reach of the children

INDICATIONS AND USAGE

apply sufficient amount to the skin and wash away with warm water

WARNINGS

・Stop using the product when you have skin problems or the product disagrees with your skin
・Stop using the product immediately and consult a dermatologist if you have redness, swelling, itching or irritation on the skin while or after using the product.
・Don't place the product in any place where it will be subjected to extremely high or low temperatures or direct sunlight.

DOSAGE AND ADMINISTRATION

for external use only